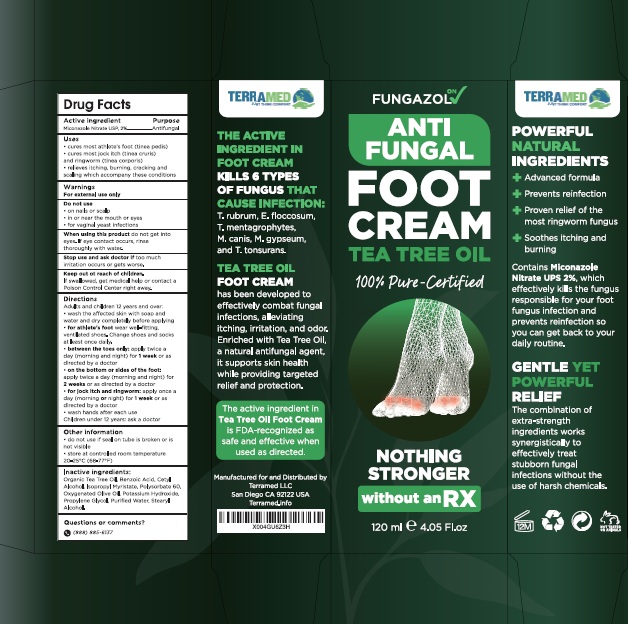 DRUG LABEL: Fungazol Athlete Foot
NDC: 83004-025 | Form: CREAM
Manufacturer: Rida LLC
Category: otc | Type: HUMAN OTC DRUG LABEL
Date: 20250528

ACTIVE INGREDIENTS: MICONAZOLE NITRATE 2 g/100 mL
INACTIVE INGREDIENTS: TEA TREE OIL; BENZOIC ACID; CETYL ALCOHOL; ISOPROPYL MYRISTATE; POLYSORBATE 60; OLIVE OIL; POTASSIUM HYDROXIDE; PROPYLENE GLYCOL; WATER; STEARYL ALCOHOL

Active Ingredient

Miconazole Nitrate USP, 2%

Purpose

Antifungal

Uses

- cures most athlete’s foot (tinea pedis)
- cures most jock itch (tinea cruris) and ringworm (tinea corporis)
- relieves itching, burning, cracking and scaling which accompany theses conditions

Warnings

For external use only

Do not use

- on nails or scalp
- in or near the mouth or eyes
- for vaginal yeast infections

When using this product do not get into eyes. If eye contact occurs, rinse thoroughly with water.

Stop use and ask a doctor if too much irritation occurs or gets worse.

Keep out of the reach of children.If swallowed, get medical help or contact a Poison Control Center right away.

Directions

Adults and children 12 years and over:

- wash affected area with soap and water and dry completely before applying
- for athlet's foo twear well-fitting, ventilated shoes. Change shoes and socks at least once daily.
- between the tose only:apply twice a day (morning and night) for 1 weekor as directed by doctor
- on the bottom or sides of the foot: apply twice a day (morning and night) for 2 weeksor as directed by doctor
- for jock itch and ringworm: apply once a day (morning ornight) for 1 weekor as directed by a doctor
- wash hands after each use
- Children under 12 years: ask a doctor

Other Information

- do not use if seal on the tube is broken or is not visible.
- store at controlled room temperature 20-25°C (68-77°F)

Inactive ingredients

Organic tea tree oil, benzoic acid, cetyl alcohol, isopropyl myristate, polysorbate 60, olive oil, potassium hydroxide, propylene glycol, water, stearyl alcohol

Questions or comments?

(888) 885-6137